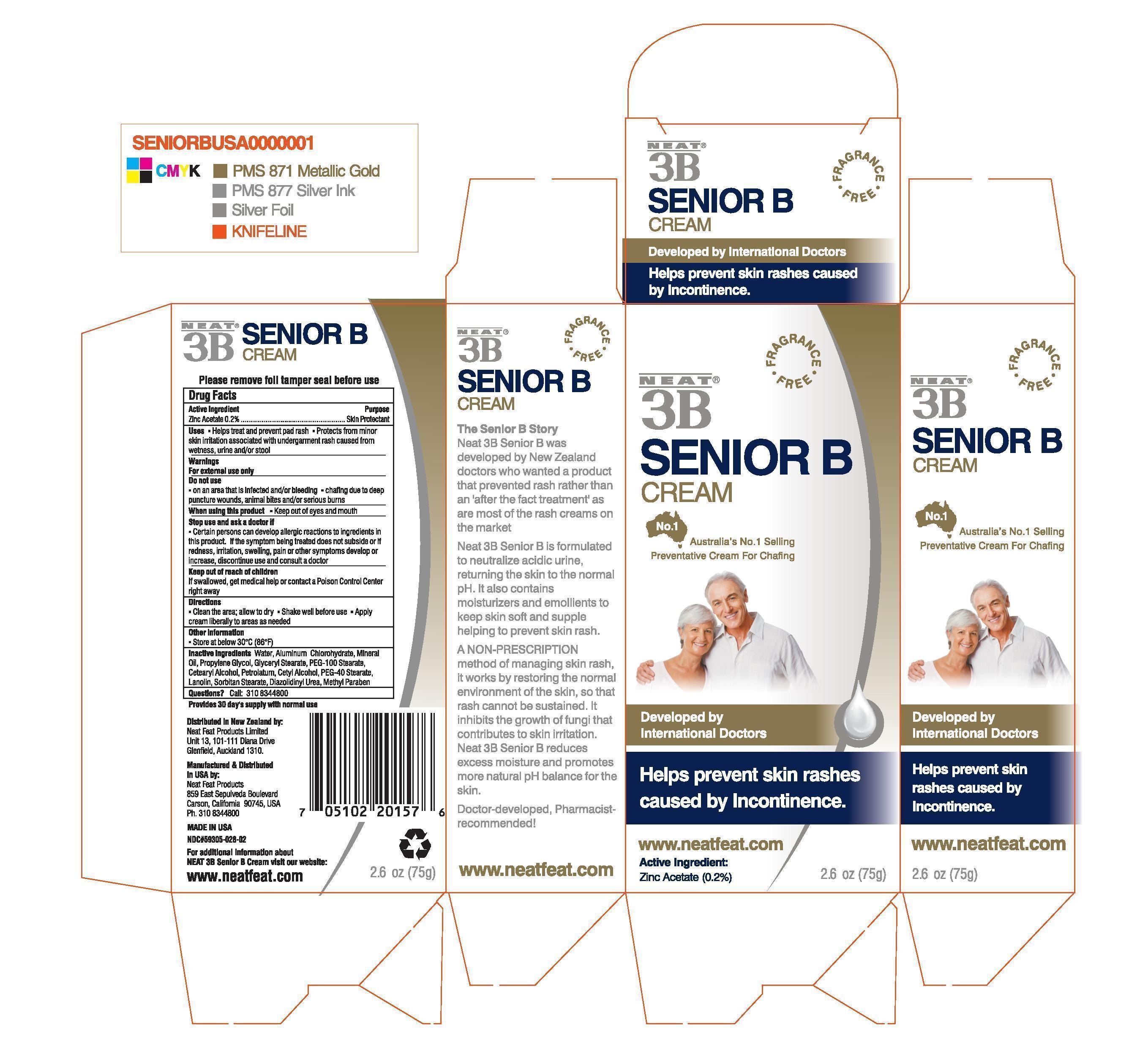 DRUG LABEL: Senior B
NDC: 59305-028 | Form: CREAM
Manufacturer: NEAT FEAT PRODUCTS
Category: otc | Type: HUMAN OTC DRUG LABEL
Date: 20130903

ACTIVE INGREDIENTS: ZINC ACETATE 1.5 g/75 g
INACTIVE INGREDIENTS: water; ALUMINUM CHLOROHYDRATE; MINERAL OIL; PROPYLENE GLYCOL; GLYCERYL MONOSTEARATE; PEG-100 STEARATE; CETOSTEARYL ALCOHOL; PETROLATUM; CETYL ALCOHOL; PEG-40 STEARATE; LANOLIN; SORBITAN MONOSTEARATE; DIAZOLIDINYL UREA; METHYLPARABEN

Active Ingredients

Zinc Acetate 0.2%

Uses

Helps treat and prevent pad rash

Protects from minor skin irritation associated with undergarment rash caused from wetness, urine and/or stool.

Keep out of reach of children

If swallowed, get medical help or contact Poison Control Center right away

INDICATIONS AND USAGE

Helps prevent skin rashes caused by Incontinence.

Warnings For external use only

Do not use On an area that is infected and/or bleeding

Chafing due to deep puncture wounds, animal bites and/or serious burns

When using this product Keep out of eyes and mouth

Stop use an ask a doctor if Certain persons can develop allergic reactions to ingredients in this product. If the symptom being treated does not subside or if redness,

Irritation, swelling, pain or other symptoms develop or increase, discontinue use and consult a doctor

Directions

Clean the area; allow to dry

Shake well before use

apply cream liberally to areas as needed

INACTIVE INGREDIENT

Inactive Ingredients: Water, Aluminum Chlorohydrate, Mineral Oil, Propylene Glycol, Glyceryl Stearate, PEG-100 Stearate, Cetearyl Alcohol, PEG-40 Stearate, Lanolin, Sorbitan Stearate, Diazolidinyl Urea, Methyl Paraben